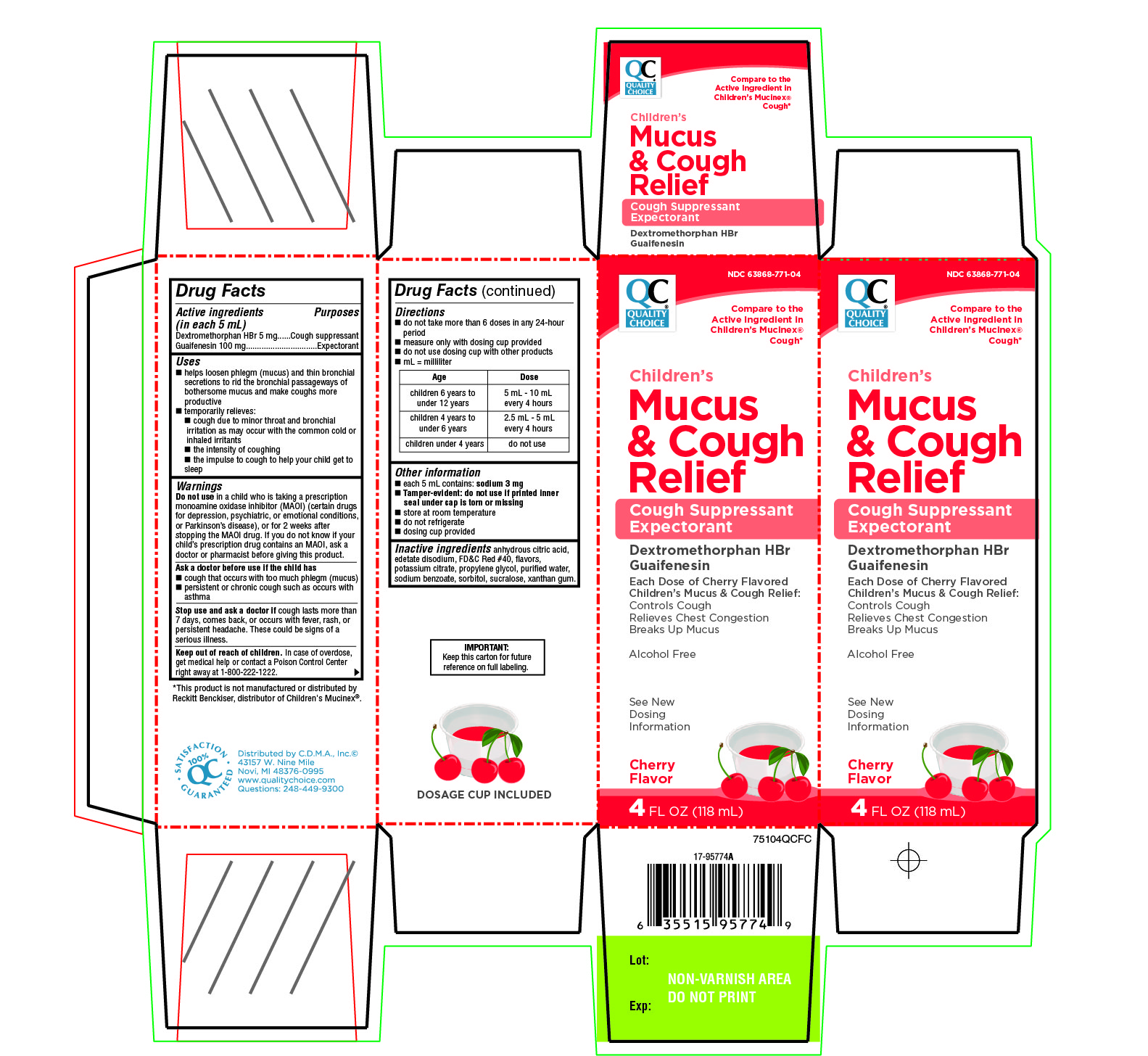 DRUG LABEL: Childrens Mucus and Cough Relief
NDC: 63868-771 | Form: LIQUID
Manufacturer: Chain Drug Manufacturing Assn
Category: otc | Type: HUMAN OTC DRUG LABEL
Date: 20251204

ACTIVE INGREDIENTS: DEXTROMETHORPHAN HYDROBROMIDE 5 mg/5 mL; GUAIFENESIN 100 mg/5 mL
INACTIVE INGREDIENTS: ANHYDROUS CITRIC ACID; EDETATE DISODIUM; FD&C RED NO. 40; POTASSIUM CITRATE; PROPYLENE GLYCOL; WATER; SODIUM BENZOATE; SORBITOL; SUCRALOSE; XANTHAN GUM

Quality Choice Children's Mucus &
Cough Relief Cherry Flavor 4 FL OZ
(118 mL)

Drug Facts

ACTIVE INGREDIENT

PURPOSE

Active ingredients (in each 5 mL) | Purposes
Dextromethorphan HBr 5 mg | Cough suppressant
Guaifenesin 100 mg | Expectorant

Uses

- helps loosen phlegm (mucus) and thin bronchial secretions to rid the bronchial passageways of bothersome mucus and make coughs more productive
- temporarily relieves:
  - cough due to minor throat and bronchial irritation as may occur with the common cold or inhaled irritants
  - the intensity of coughing
  - the impulse to cough to help your child get to sleep

Warnings

DO NOT USE

Do not usein a child who is taking a prescription monoamine oxidase inhibitor (MAOI) (certain drugs for depression, psychiatric, or emotional conditions, or Parkinson's disease), or for 2 weeks after stopping the MAOI drug. If you do not know if your child's prescription drug contains an MAOI, ask a doctor or pharmacist before giving this product.

Ask a doctor before use if the child has

- cough that occurs with too much phlegm (mucus)
- persistent or chronic cough such as occurs with asthma

Stop use and ask a doctor ifcough lasts more than 7 days, comes back, or occurs with fever, rash, or persistent headache. These could be signs of a serious illness.

Keep out of reach of children.In case of overdose, get medical help or contact a Poison Control Center right away at 1-800-222-1222.

Directions

- do not take more than 6 doses in any 24-hour period
- measure only with dosing cup provided
- do not use dosing cup with other products
- mL = milliliter

Age | Dose
children 6 years to under 12 years | 5 mL – 10 mL every 4 hours
children 4 years to under 6 years | 2.5 mL – 5 mL every 4 hours
children under 4 years | do not use

Other information

- each 5 mL contains: sodium 3 mg
- Tamper -evident: do not use if printed inner seal under cap is torn or missing
- store at room temperature
- do not refrigerate
- dosing cup provided

Inactive ingredients

Anhydrous citric acid, edetate disodium, FD&C Red#40, flavors, potassium citrate, propylene glycol, purified water, sodium benzoate, sorbitol, sucralose, xanthan gum

PRINCIPAL DISPLAY PANEL - 118 mL Bottle Carton

NDC 63868-771-04

Compare to the Active ingredient in Children’s Mucinex Cough*

Children's

Mucus &Cough Relief

Cough Suppressant

Expectorant

Dextromethorphan HBr

Guaifenesin

Each Dose of Cherry Flavored

Children's

Mucus & Cough Relief:

Controls Cough
Relieves Chest Congestion
Breaks up Mucus

Alcohol-free

See New Dosing information

Cherry
Flavor

4 FL OZ
(118 mL)

IMPORTANT: Keep this carton for future reference on full labeling.

DOSAGE CUP INCLUDED

Distributed by C.D.M.A., Inc©

43157 W. Nine Mile

Novi, MI 48376-0995

www.qualitychoice.com

Questions: 248-449-9300

*This product is not manufactured or distributed by Reckitt Benckiser, distributor of Children’s Mucinex.®

QC 100% Satisfaction Guaranteed.